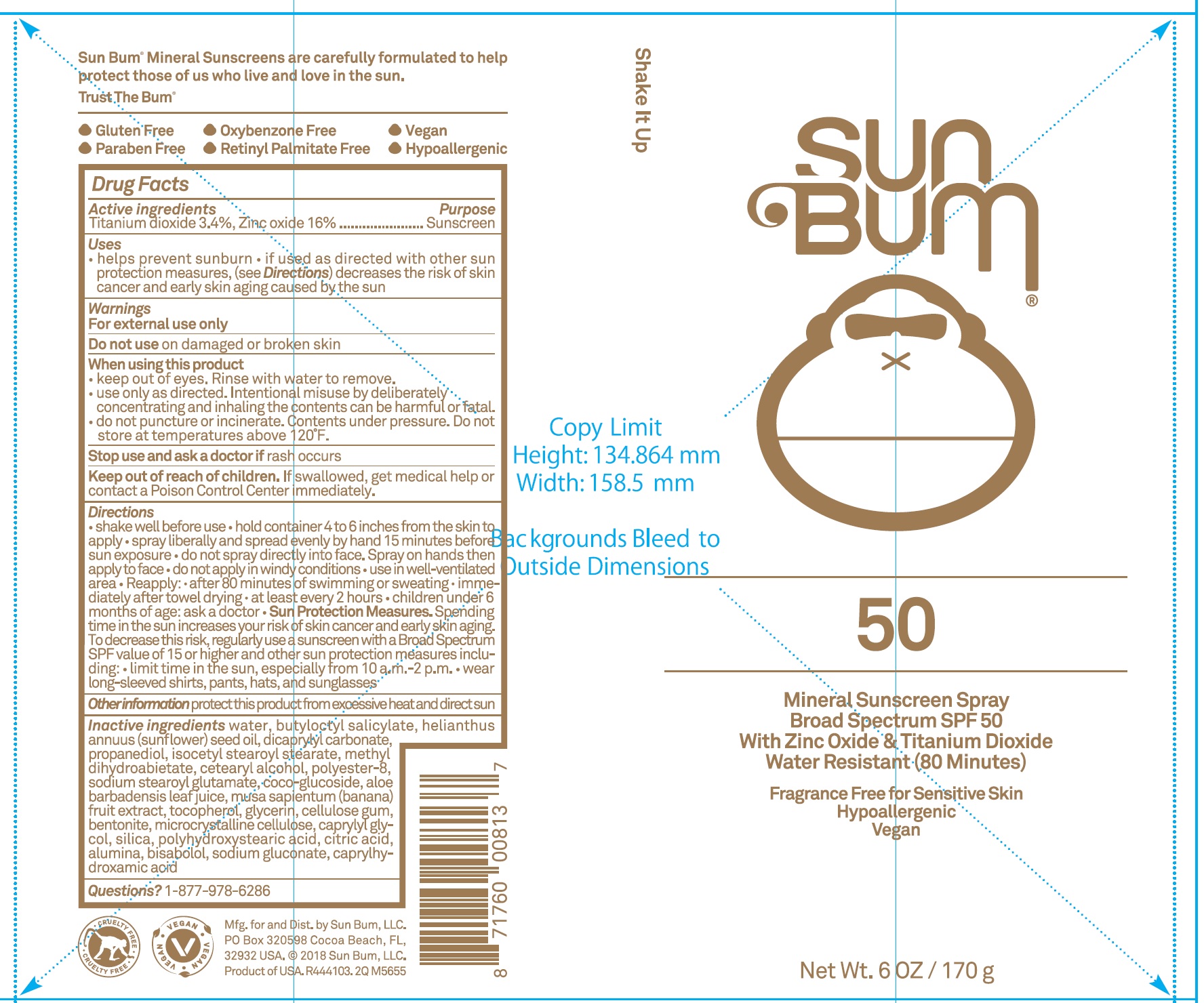 DRUG LABEL: Sun Bum Mineral Sunscreen Broad Spectrum SPF 50
NDC: 69039-624 | Form: LIQUID
Manufacturer: Sun Bum LLC
Category: otc | Type: HUMAN OTC DRUG LABEL
Date: 20220204

ACTIVE INGREDIENTS: TITANIUM DIOXIDE 34 mg/1 g; ZINC OXIDE 160 mg/1 g
INACTIVE INGREDIENTS: WATER; BUTYLOCTYL SALICYLATE; SUNFLOWER OIL; DICAPRYLYL CARBONATE; PROPANEDIOL; ISOCETYL STEAROYL STEARATE; METHYL DIHYDROABIETATE; CETOSTEARYL ALCOHOL; SODIUM STEAROYL GLUTAMATE; COCO GLUCOSIDE; ALOE VERA LEAF; BANANA; TOCOPHEROL; GLYCERIN; CARBOXYMETHYLCELLULOSE SODIUM, UNSPECIFIED; BENTONITE; MICROCRYSTALLINE CELLULOSE; CAPRYLYL GLYCOL; SILICON DIOXIDE; CITRIC ACID MONOHYDRATE; ALUMINUM OXIDE; LEVOMENOL; SODIUM GLUCONATE; CAPRYLHYDROXAMIC ACID

Sun Bum Mineral Sunscreen Spray Broad Spectrum SPF 50

Active ingredient

Titanium dioxide 3.4%

Zinc oxide 16%

Purpose

Sunscreen

Uses

- helps prevent sunburn
- if used as directed with other sun protection measures (see Directions), decreases the risk of skin cancer and early skin aging caused by the sun

Warnings

- For external use only

Do not use

- on damaged or broken skin

When using this product

- keep out of eyes. Rinse with water to remove.
- use only as directed. Intentional misuse by deliberately concentrating and inhaling the contents can be harmful or fatal.
- do not puncture or incinerate. Contents under pressure. Do not store at room temperature above 120°F.

Stop use and ask a doctor if

- rash occurs

Keep out of reach of children.

- If swallowed, get medical help or contact a Poison Control Center immediately.

Directions

- shake well before use
- hold container 4 to6 inches from the skin to apply
- spray liberally and spread evenly by hand 15 minutes before sun exposure
- do not spray directly into face. Spray on hands then apply to face
- do not apply in windy conditions
- use in well-ventilated area
- Reapply:
- after 80 minutes of swimming or sweating, immediately after towel drying
- at least every 2 hours.
- children under 6 months of age: ask a doctor.
- Sun Protections Measures- Spending time in the sun increases your risk of skin cancer and early skin aging. To decrease this risk, regurlarly use a sunscreen with a Broad Spectrum SPF value of 15 or higher and other sun protection measures including:
- limit time in the sun, especially from 10 a.m. - 2 p.m.
- wear long-sleeved shirts, pants, hats, and sunglasses

Other information

protect this product from excessive heat and direct sun.

Inactive ingredients

water, butyloctyl salicylat, helianthus annus (sunflower) seed oil, dicaprylyl carbonate, propanediol, isocetyl stearoyl stearate, methyl dihydroabietate, cetearyl alcohol, polyester-8, sodium stearoyl glutamate, coco-glucoside, aloe barbadensis leaf juice, musa sapientum (banana) fruit extract, tocopherol, glycerin, cellulose gum,bentonite, microcrystalline cellulose, caprylyl glycol, silica, polyhydroxystearic acid, citric acid, alumina, bisabolol, sodium gluconate, caprylhydroxamic acid

Questions?

1-877-978-6286